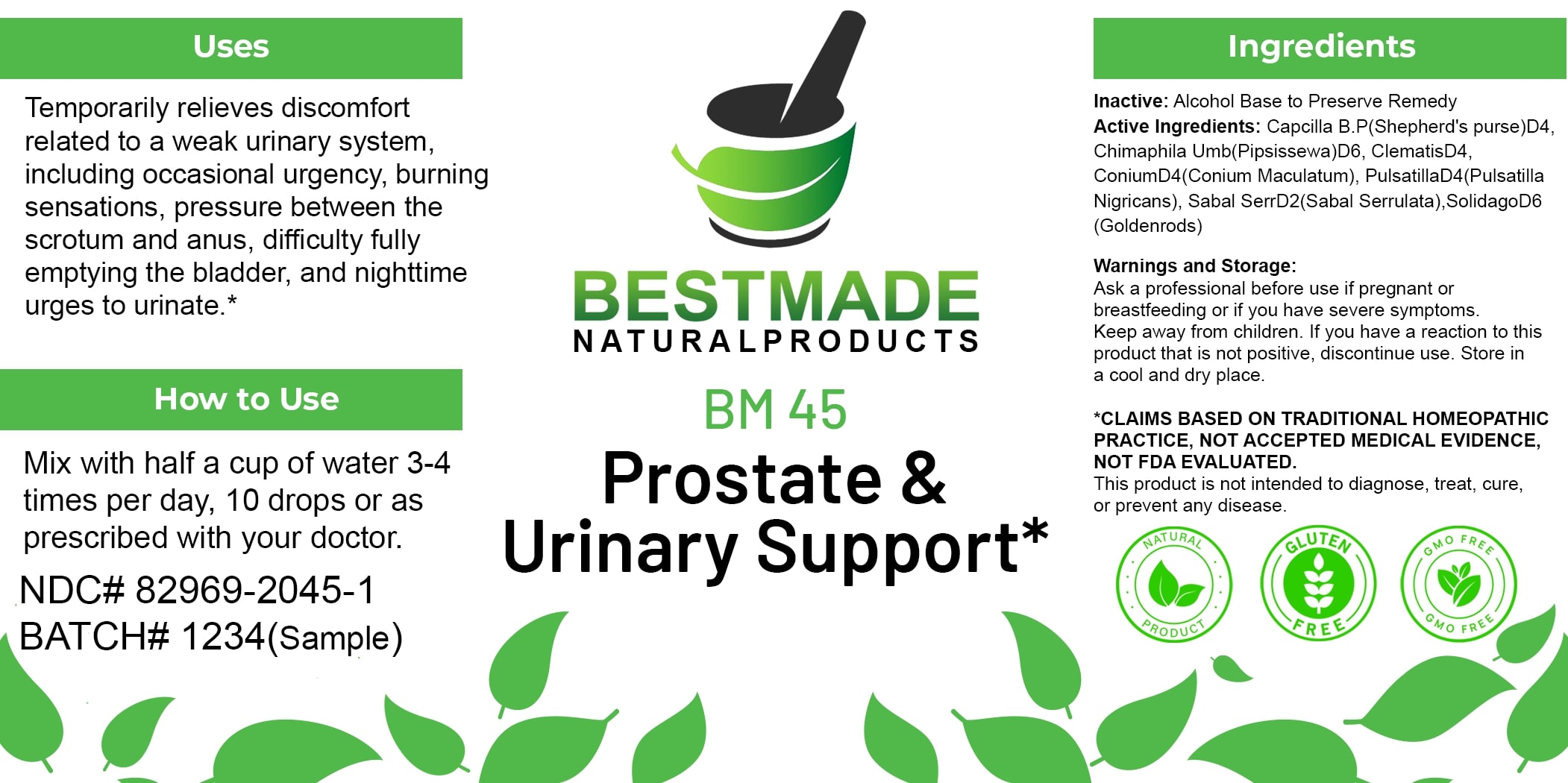 DRUG LABEL: Bestmade Natural Products BM45
NDC: 82969-2045 | Form: LIQUID
Manufacturer: Bestmade Natural Products
Category: homeopathic | Type: HUMAN OTC DRUG LABEL
Date: 20250123

ACTIVE INGREDIENTS: CHIMAPHILA UMBELLATA 30 [hp_C]/30 [hp_C]; PULSATILLA PRATENSIS 30 [hp_C]/30 [hp_C]; CAPSELLA BURSA-PASTORIS 30 [hp_C]/30 [hp_C]; CONIUM MACULATUM FLOWERING TOP 30 [hp_C]/30 [hp_C]; SAW PALMETTO 30 [hp_C]/30 [hp_C]; CLEMATIS RECTA FLOWERING TOP 30 [hp_C]/30 [hp_C]; SOLIDAGO VIRGAUREA FLOWERING TOP 30 [hp_C]/30 [hp_C]
INACTIVE INGREDIENTS: ALCOHOL 30 [hp_C]/30 [hp_C]

BM45

DOSAGE AND ADMINISTRATION

How to Use

Mix with half a cup of water 3-4 times per day, 10 drops or as prescribed with your doctor.

Uses

Temporarily relieves discomfort related to a weak urinary system, including occasional urgency, burning sensations, pressure between the scrotum and anus, difficulty fully emptying the bladder, and nighttime urges to urinate.*

*CLAIMS BASED ON TRADITIONAL HOMEOPATHIC PRACTICE, NOT ACCEPTED MEDICAL EVIDENCE, NOT FDA EVALUATED.

This product is not intended to diagnose, treat, cure, or prevent any disease.

Uses

Temporarily relieves discomfort related to a weak urinary system, including occasional urgency, burning sensations, pressure between the scrotum and anus, difficulty fully emptying the bladder, and nighttime urges to urinate.*

*CLAIMS BASED ON TRADITIONAL HOMEOPATHIC PRACTICE, NOT ACCEPTED MEDICAL EVIDENCE, NOT FDA EVALUATED.

This product is not intended to diagnose, treat, cure, or prevent any disease.

INACTIVE INGREDIENT

Ingredients

Inactive: Alcohol Base to Preserve Remedy

ACTIVE INGREDIENT

Active Ingredients: Capsella B.P(Shepherd's purse) D4, Chimaphila Umb(Pipsissewa) D6, Clematis D4, Conium D4 (Conium Maculatum), Pulsatilla D4 (Pulsatilla Nigricans), Sabal Serr D2 (Sabal Serrulata), Solidago D6 (Goldenrods)

KEEP OUT OF REACH OF CHILDREN

Warnings and Storage:

Ask a professional before use if pregnant or breastfeeding or if you have severe symptoms. Keep away from children. If you have a reaction to this product that is not positive, discontinue use. Store in a cool and dry place.

Warnings and Storage:

Ask a professional before use if pregnant or breastfeeding or if you have severe symptoms. Keep away from children. If you have a reaction to this product that is not positive, discontinue use. Store in a cool and dry place.

*CLAIMS BASED ON TRADITIONAL HOMEOPATHIC PRACTICE, NOT ACCEPTED MEDICAL EVIDENCE, NOT FDA EVALUATED.

This product is not intended to diagnose, treat, cure, or prevent any disease.

Entire package label